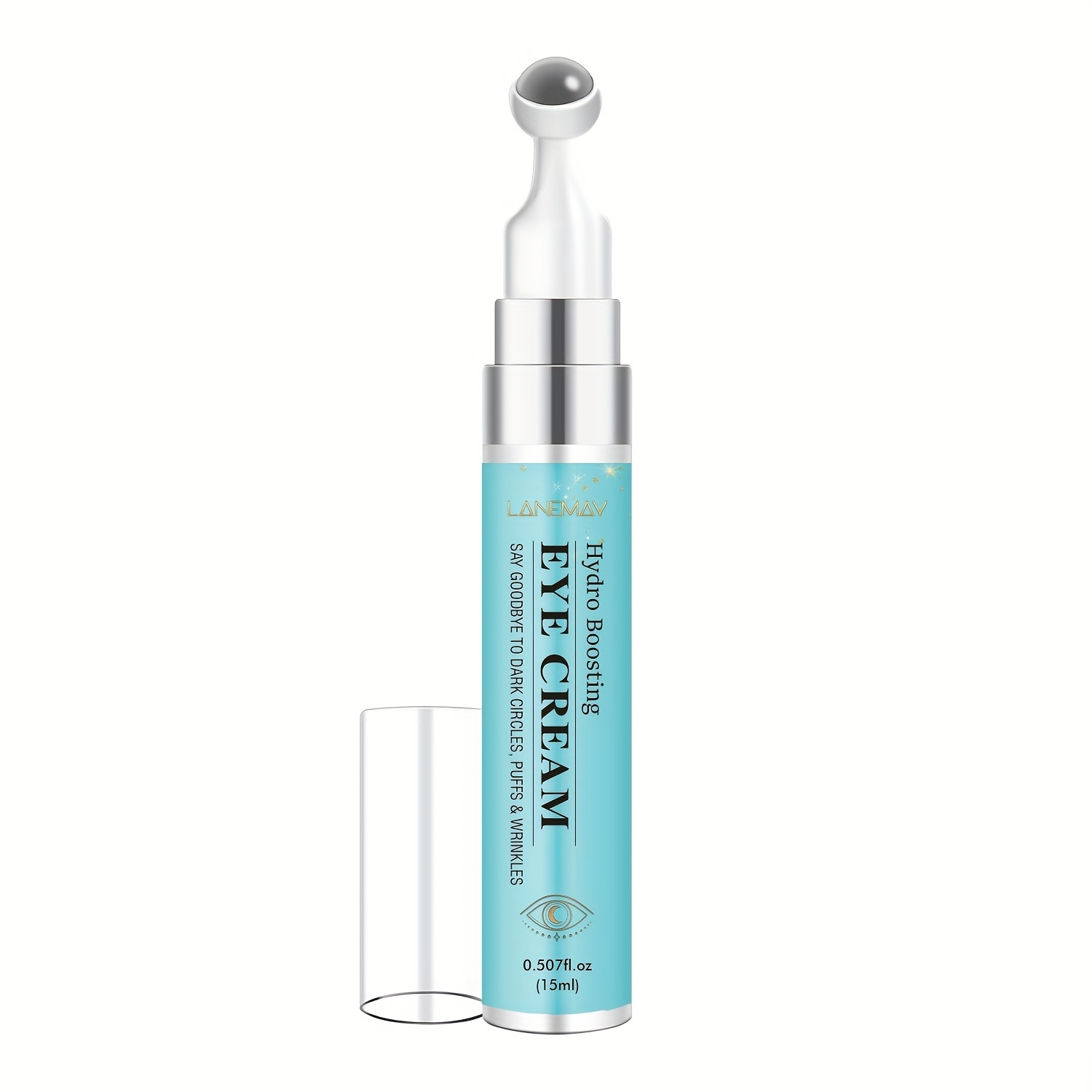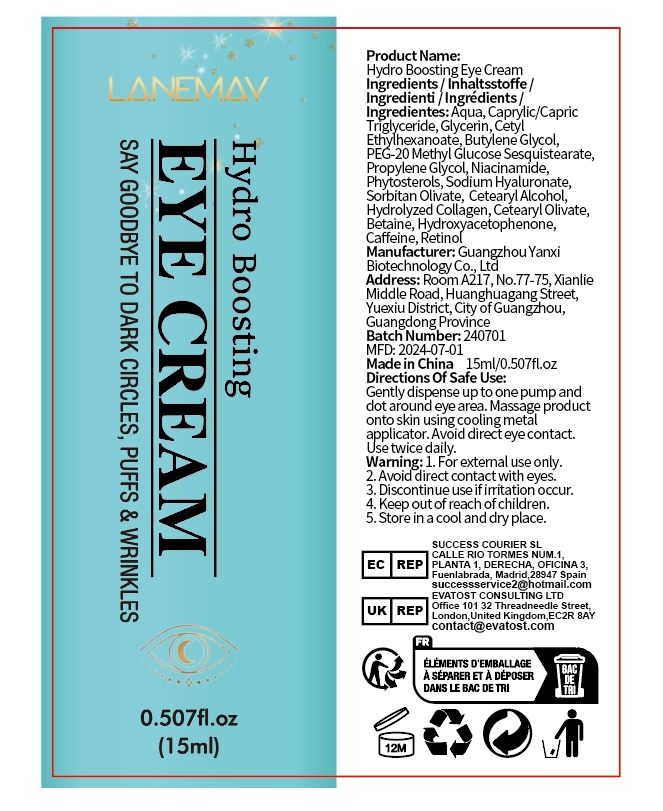 DRUG LABEL: Hydro Boosting Eye cream
NDC: 84025-167 | Form: CREAM
Manufacturer: Guangzhou Yanxi Biotechnology Co.. Ltd
Category: otc | Type: HUMAN OTC DRUG LABEL
Date: 20240826

ACTIVE INGREDIENTS: GLYCERIN 5 mg/15 mL; BUTYLENE GLYCOL 3 mg/15 mL
INACTIVE INGREDIENTS: WATER

DOSAGE AND ADMINISTRATION

For reducing dark circles around eyes and keeping eye skin healthy

WARNINGS

keep out of children

INACTIVE INGREDIENT

AQUA

INDICATIONS AND USAGE

For daily eye skin care

keep out of children

PURPOSE

Effectively reduces wrinkles around eyes and fine lines